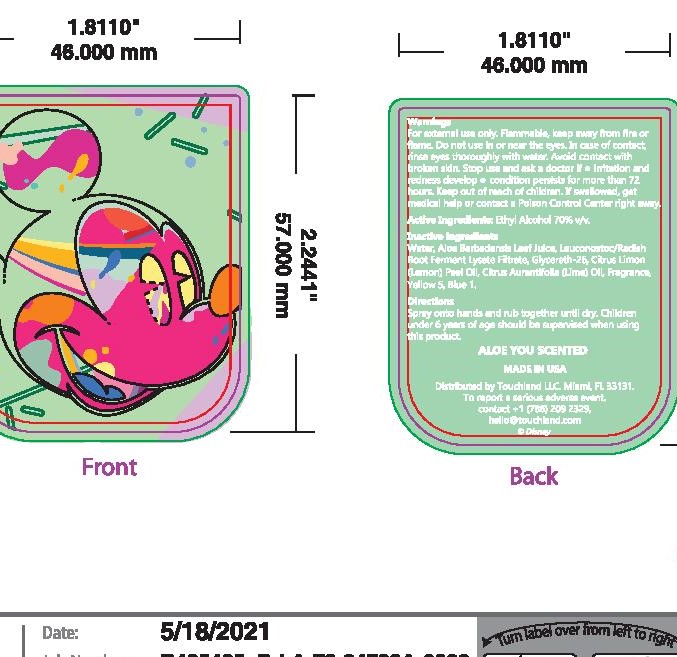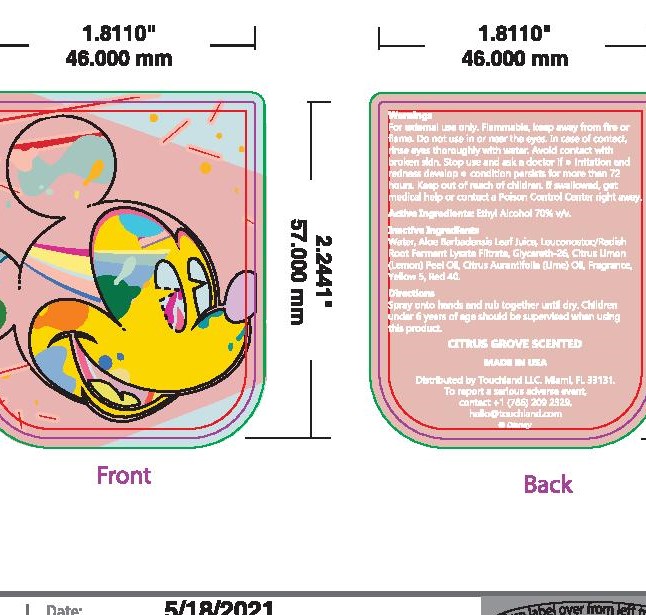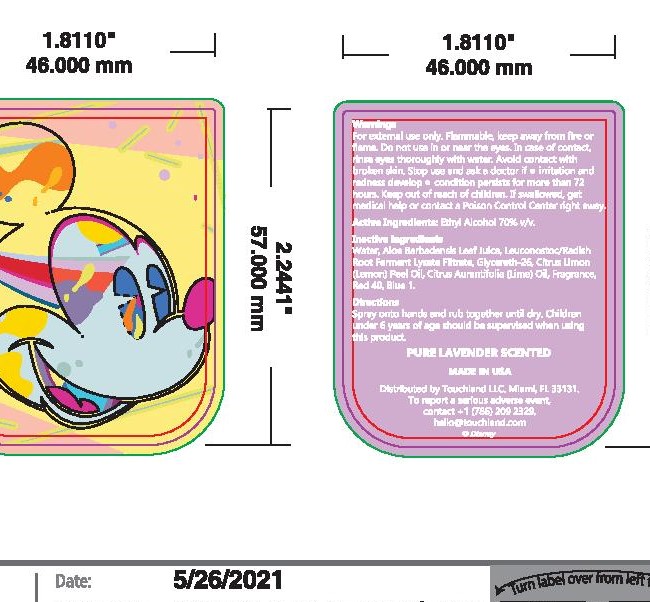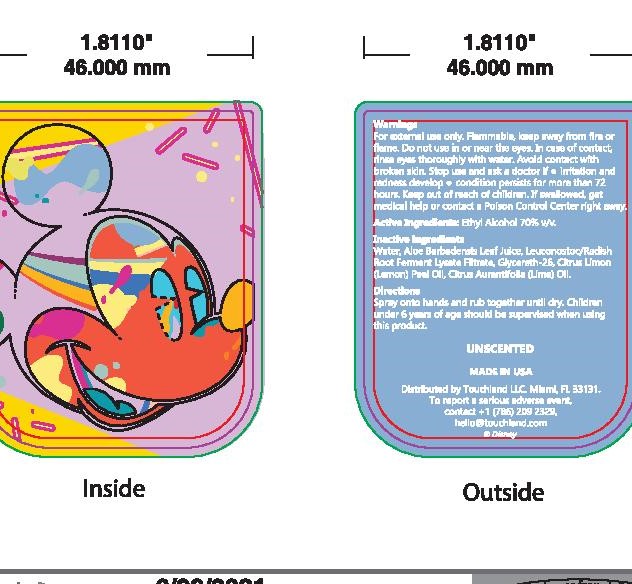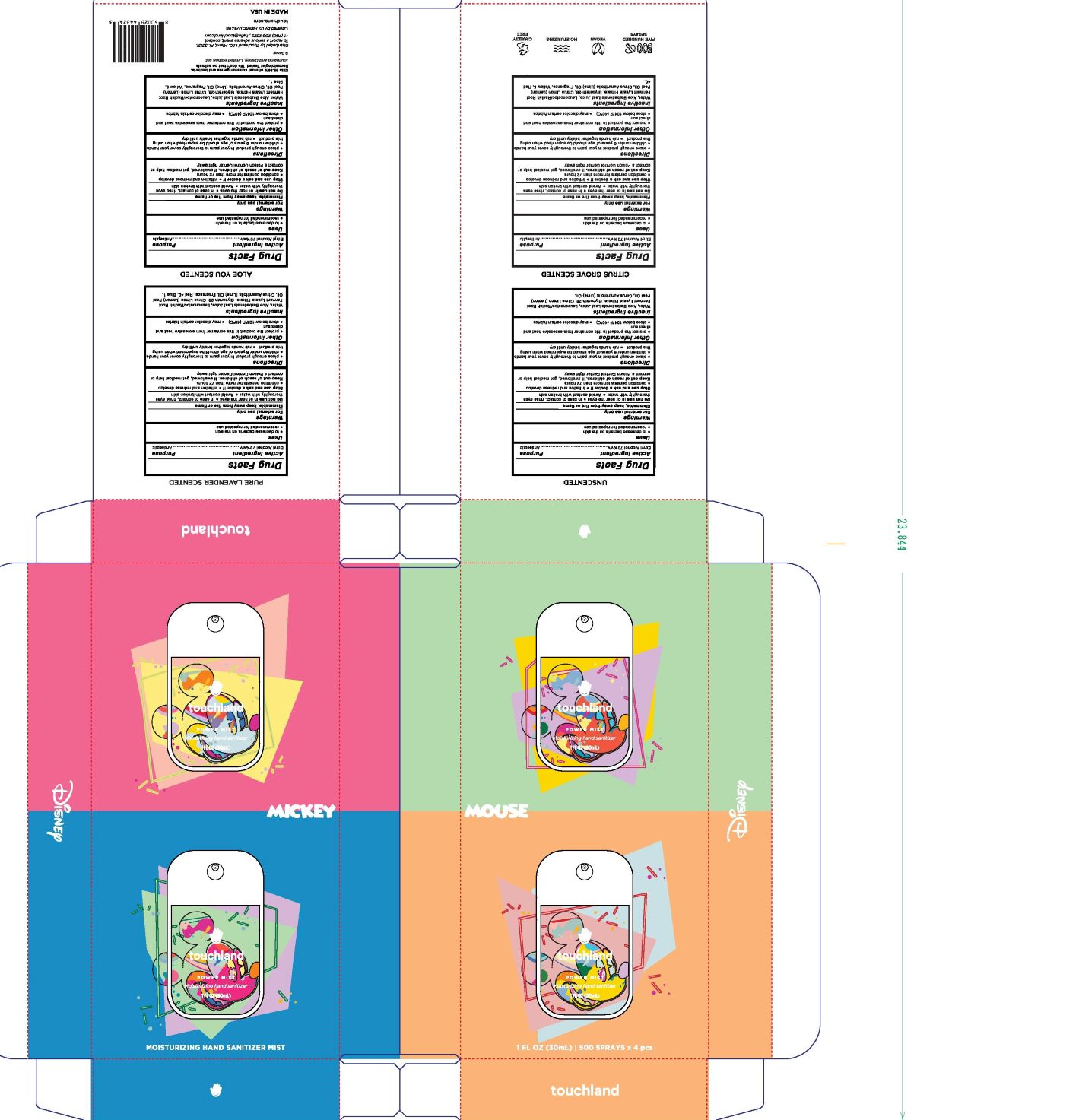 DRUG LABEL: Disney 4 pack
NDC: 76150-327 | Form: SPRAY
Manufacturer: Bell International Laboratories, Inc
Category: otc | Type: HUMAN OTC DRUG LABEL
Date: 20210823

ACTIVE INGREDIENTS: ALCOHOL 70 mL/100 mL
INACTIVE INGREDIENTS: GLYCERETH-26; WATER; LEMON OIL; FD&C BLUE NO. 1; FD&C RED NO. 40; ALOE VERA LEAF; LEUCONOSTOC/RADISH ROOT FERMENT FILTRATE; LIME OIL; FD&C YELLOW NO. 5

Touchland Disney Hand Sanitizer Spray 4-pack (4 different scents)

Active Ingredient

Ethyl Alcohol 70% v/v

Purpose

Antiseptic

Uses

To decrease bacteria on the skin

Recommended for repeated use

Warnings

For external use only

Flammable, keep away from fire or flame

Do not use in or near the eyes. In case of contact, rinse eyes thoroughly with water. Avoid contact with broken skin

Stop use and ask a doctor if irritation and redness develop

Condition persists for more than 72 hours

Keep out of reach of children. If swallowed, get medical help or contact a Poison Control Center right away

Directions

Place enough product in your palm to thoroughly cover your hands

Children under 6 years of age should be supervised when using this product

Rub hands together briskly until dry

Inactive Ingredients

Water, Aloe Barbadensis Leaf Juice, Leuconostoc/Radish Root Ferment Lysate Filtrate, Glycereth-26, Citrus Limon (Lemon) Peel Oil, Citrus Aurantifolia (Lime) Oil

May contain:

Fragrance, Yellow 5, Blue 1, Red 40

Other Information

Protect the product in this container from excessive heat and direct sun

Store below 104F (40C)

May discolor certain fabrics